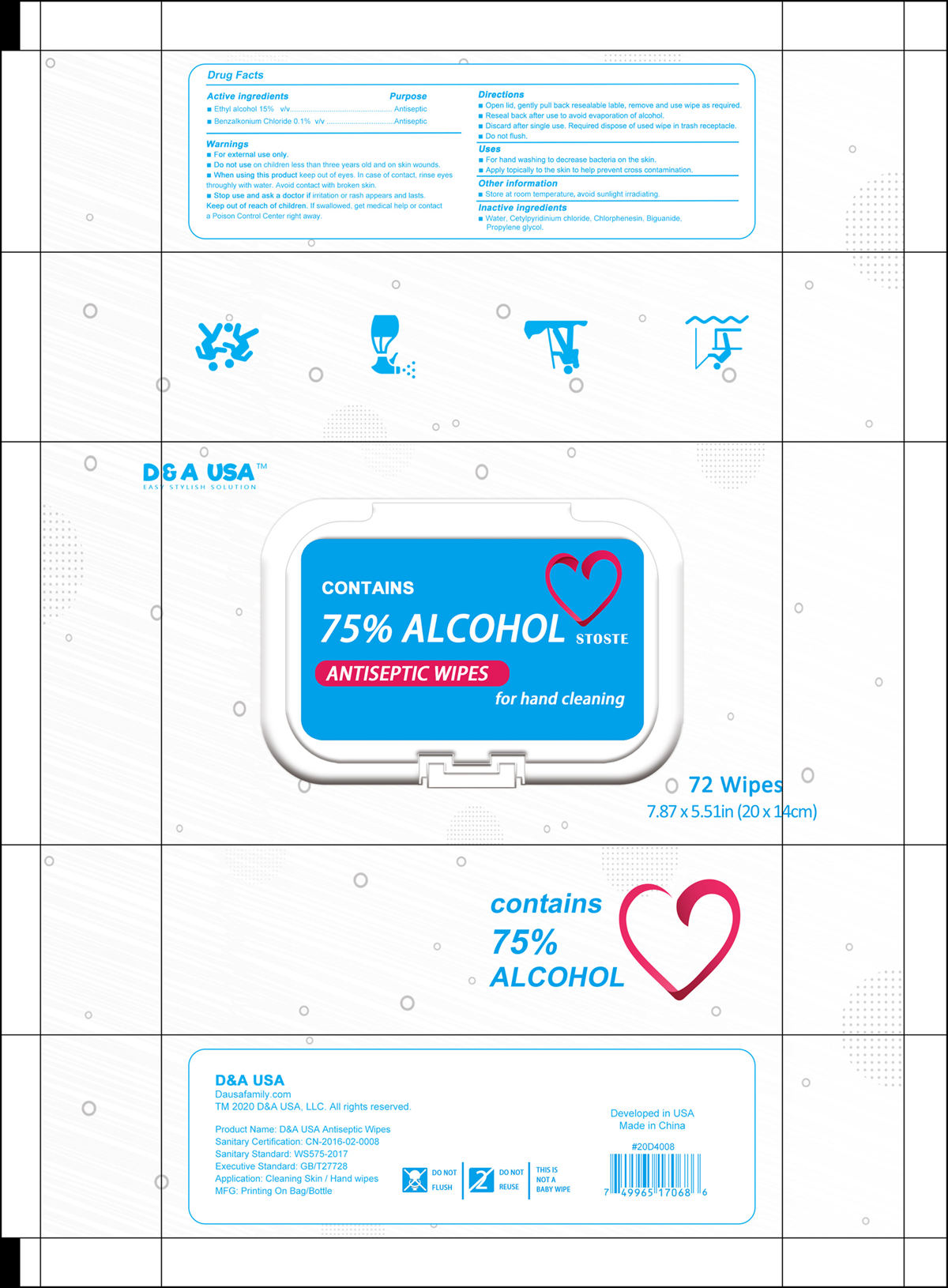 DRUG LABEL: Antiseptic Wipes
NDC: 80956-001 | Form: CLOTH
Manufacturer: D&A USA, LLC
Category: otc | Type: HUMAN OTC DRUG LABEL
Date: 20211228

ACTIVE INGREDIENTS: ALCOHOL 15 mL/100 g; BENZALKONIUM CHLORIDE 0.1 g/100 g
INACTIVE INGREDIENTS: BIGUANIDE; PROPYLENE GLYCOL; WATER; CETYLPYRIDINIUM CHLORIDE; CHLORPHENESIN

Antiseptic Wipes

Active Ingredients

Ethyl alcohol 15%. v/v

Benzalkonium Chloride 0.1%. v/v

Purpose

Antiseptic

Warnings

- For external use only.

Do not use

on children less than three years old and on skin wounds.

When using this product

Keep out of eyes. In case of contact, rinse eyes thoroughly with water. Avoid contact with broken skin.

Stop use and ask a doctor if

irritation or rash appears and lasts.

Keep out of reach of children

If swallowed, get medical help or contact a Poison Control Center right away.

Directions

- Open lid, gently pull back resealable label, remove and use wipe as required.
- Reseal back after use to avoid evaporation of alcohol.
- Discard after single use Required dispose of used wipe in trash receptable.
- Do not flush.

Uses

- For hand washing to decrease bacteria on the skin.
- Apply topically to the skin to help prevent cross contamination.

Other information

Store at room temperature, avoid sunlight irradiating.

Inactive ingredients

Water, Cetylpyridinium chloride, Chlorphenesin, Biguanide, Propylene glycol